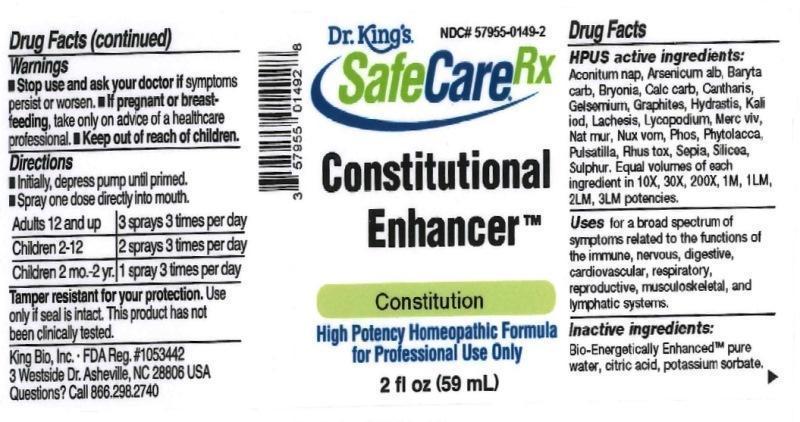 DRUG LABEL: Constitutional Enhancer
NDC: 57955-0149 | Form: LIQUID
Manufacturer: King Bio Inc.
Category: homeopathic | Type: HUMAN OTC DRUG LABEL
Date: 20161109

ACTIVE INGREDIENTS: ACONITUM NAPELLUS 10 [hp_X]/59 mL; ARSENIC TRIOXIDE 10 [hp_X]/59 mL; BARIUM CARBONATE 10 [hp_X]/59 mL; BRYONIA ALBA ROOT 10 [hp_X]/59 mL; OYSTER SHELL CALCIUM CARBONATE, CRUDE 10 [hp_X]/59 mL; LYTTA VESICATORIA 10 [hp_X]/59 mL; GELSEMIUM SEMPERVIRENS ROOT 10 [hp_X]/59 mL; GRAPHITE 10 [hp_X]/59 mL; GOLDENSEAL 10 [hp_X]/59 mL; POTASSIUM IODIDE 10 [hp_X]/59 mL; LACHESIS MUTA VENOM 10 [hp_X]/59 mL; LYCOPODIUM CLAVATUM SPORE 10 [hp_X]/59 mL; MERCURY 10 [hp_X]/59 mL; SODIUM CHLORIDE 10 [hp_X]/59 mL; STRYCHNOS NUX-VOMICA SEED 10 [hp_X]/59 mL; PHOSPHORUS 10 [hp_X]/59 mL; PHYTOLACCA AMERICANA ROOT 10 [hp_X]/59 mL; PULSATILLA VULGARIS 10 [hp_X]/59 mL; TOXICODENDRON PUBESCENS LEAF 10 [hp_X]/59 mL; SEPIA OFFICINALIS JUICE 10 [hp_X]/59 mL; SILICON DIOXIDE 10 [hp_X]/59 mL; SULFUR 10 [hp_X]/59 mL
INACTIVE INGREDIENTS: WATER; ANHYDROUS CITRIC ACID; POTASSIUM SORBATE

Constitutional Enhancer™

ACTIVE INGREDIENT

Drug Facts__________________________________________________________________________________________________________

HPUS active ingredients: Aconitum napellus, Arsenicum album, Baryta carbonica, Bryonia, Calcarea carbonica, Cantharis, Gelsemium sempervirens, Graphites, Hydrastis canadensis, Kali iodatum, Lachesis mutus, Lycopodium clavatum, Mercurius vivus, Mercurius vivus, Nux vomica, Phosphorus, Phytolacca decandra, Pulsatilla, Rhus toxicodendron, Sepia, Silicea, Sulphur. Equal volumes of each ingredient in 10X, 30X, 100X, 1M, 1LM, 2LM, 3LM potencies.

INDICATIONS AND USAGE

Uses for a broad spectrum of symptoms related to the functions of the immune, nervous, digestive, cardiovascular, respiratory, reproductive, musculoskeletal, and lymphatic systems.

Inactive Ingredients:

Bio-Energetically Enhanced™ pure water, citric acid and potassium sorbate.

Warnings

- Stop use and ask your doctor if symptoms persist or worsen.
- If pregnant or breast-feeding, take only on advice of a healthcare professional.

- Keep out of reach of children.

Directions

- Initially, depress pump until primed.
- Spray one dose directly into mouth.
- Adults 12 and up: 3 sprays 3 times per day
- Children 2-12: 2 sprays 3 times per day
- Children 2mo-2yr: 1 spray 3 times per day

OTHER SAFETY INFORMATION

Tamper resistant for your protection. Use only if safety seal is intact. This product has not been independently tested.

PURPOSE

Uses for a broad spectrum of symptoms related to the functions of the immune, nervous, digestive, cardiovascular, respiratory, reproductive, musculoskeletal, and lymphatic systems.